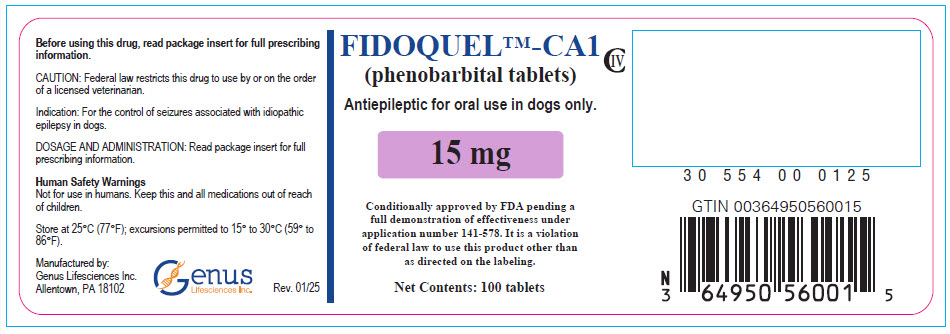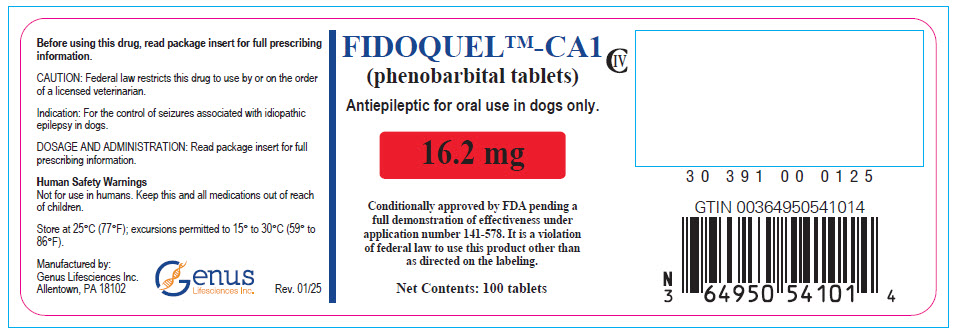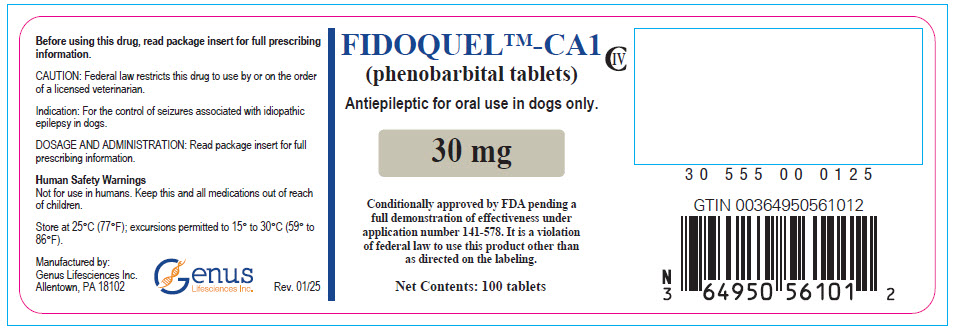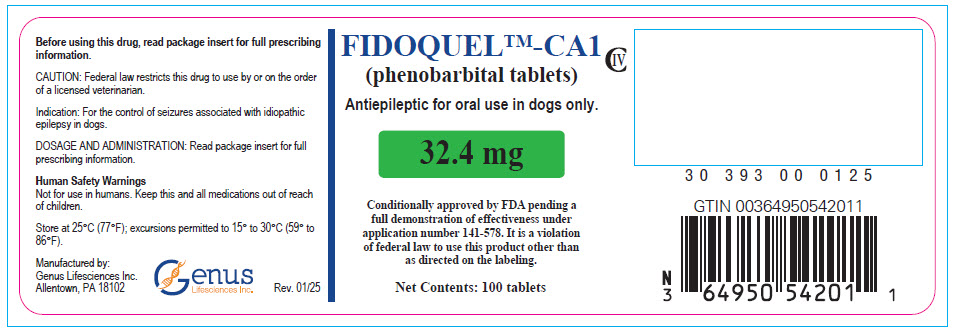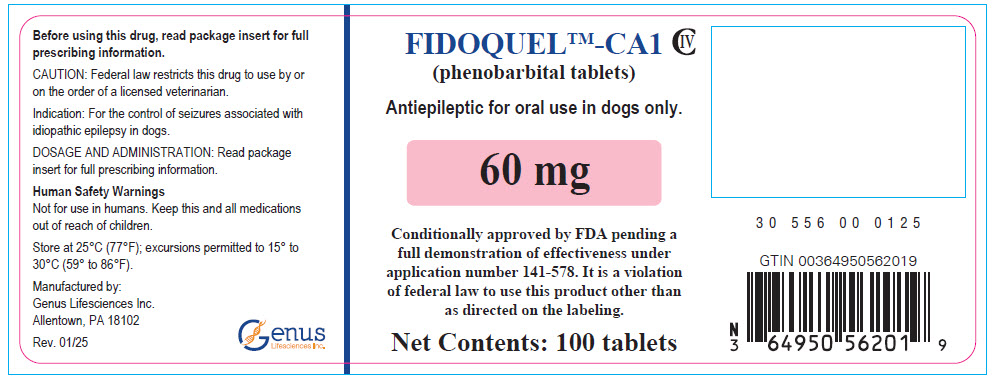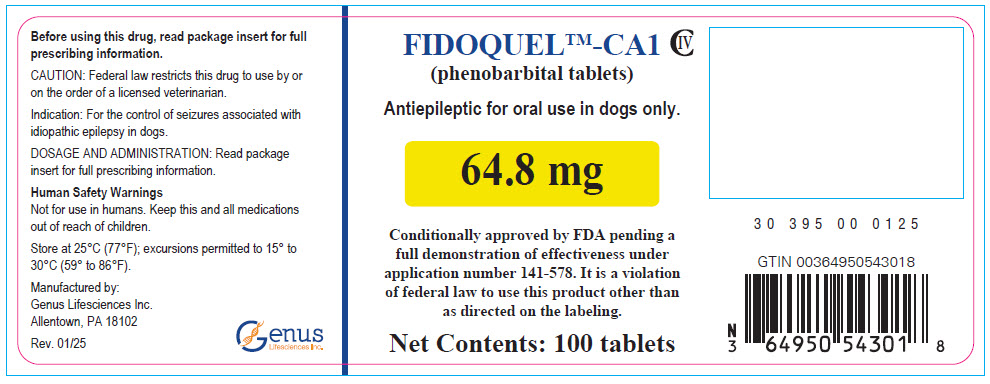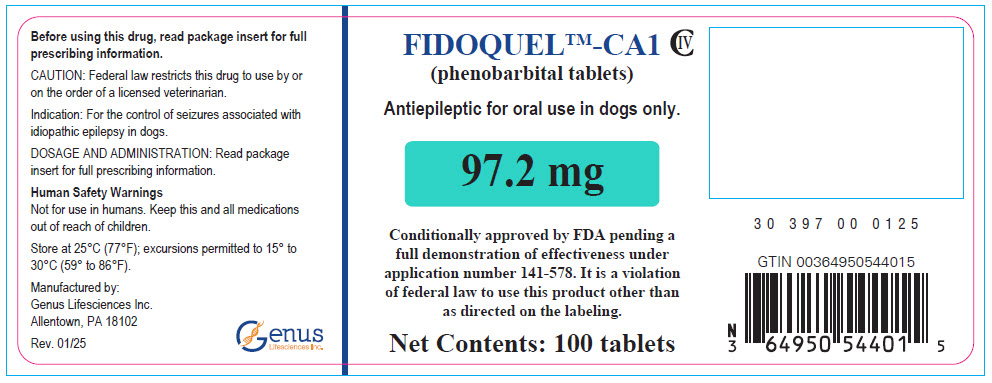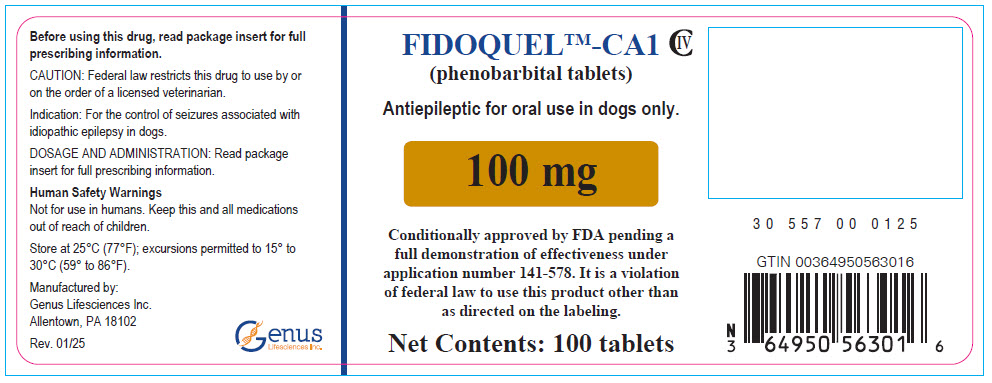 DRUG LABEL: FIDOQUEL-CA1
NDC: 64950-560 | Form: TABLET
Manufacturer: Genus Lifesciences
Category: animal | Type: PRESCRIPTION ANIMAL DRUG LABEL
Date: 20250410
DEA Schedule: CIV

ACTIVE INGREDIENTS: PHENOBARBITAL 15 mg/1 1
INACTIVE INGREDIENTS: SILICON DIOXIDE; LACTOSE MONOHYDRATE; MAGNESIUM STEARATE; MICROCRYSTALLINE CELLULOSE; SODIUM STARCH GLYCOLATE TYPE A

FIDOQUEL™-CA1
(phenobarbital tablets)

Antiepileptic for use in dogs only.

Conditionally approved by FDA pending a full demonstration of effectiveness under application number 141-578.

It is a violation of Federal law to use this product in a manner other than directed on the labeling.

GENERAL PRECAUTIONS

CAUTION: Federal law restricts this drug to use by or on the order of a licensed veterinarian. Use only as directed.

DESCRIPTION:

FIDOQUEL™-CA1 is an unflavored, bisected tablet that contains phenobarbital. Phenobarbital is white, odorless, small crystals or white crystalline powder with a bitter taste. The molar mass of phenobarbital is 232.235 g/mol, with solubility in water, alcohol, ether, and in fixed alkali hydroxides and carbonates.

INDICATION:

FIDOQUEL™-CA1 (phenobarbital tablets) are indicated for the control of seizures associated with idiopathic epilepsy in dogs.

DOSAGE AND ADMINISTRATION: FIDOQUEL™-CA1 is given orally twice a day at the minimum dosage of 2.5 mg/kg and may be titrated to effect to a maximum dosage of 5 mg/kg. The dosage of FIDOQUEL™-CA1 should be adjusted based on monitoring the clinical response of the individual patient. FIDOQUEL™-CA1 should be dosed with food.

All split tablets should be used within 90 days.

CONTRAINDICATIONS:

FIDOQUEL™-CA1 should not be used in animals with a history of hypersensitivity to phenobarbital.

WARNINGS:

Human Safety Warnings

Not for use in humans. Keep this and all medications out of reach of children. Because phenobarbital may cause developmental effects, women who are pregnant or may become pregnant should handle and administer FIDOQUEL™-CA1 with caution.

Human User Safety While Handling FIDOQUEL™ – CA1

Mucous Membrane Contact, Eye Contact, or Accidental Ingestion:

In case of accidental ingestion, skin reaction, or eye exposure, contact a physician immediately.

If accidental eye contact or mucous membrane exposure occurs, rinse the exposed area thoroughly.

Skin Contact:

Users should wash skin exposed to the drug, including washing their hands thoroughly after contacting the drug.

Drug Abuse, Addiction, and Diversion

Controlled Substance:

FIDOQUEL™-CA1 contains phenobarbital, a Schedule IV controlled substance.

Abuse: Phenobarbital is a barbiturate and a central nervous system (CNS) depressant with a potential for misuse, abuse, and addiction. Abuse is defined as the intentional, non-therapeutic use of a drug, even once, to achieve a desired psychological or physiological effect. Misuse is the intentional use, for therapeutic purposes, of a drug by an individual in a way other than prescribed by a health care provider. Drug addiction is a cluster of behavioral, cognitive, and physiological phenomena that may include a strong desire to take the drug, difficulties in controlling drug use (e.g., continuing drug use despite harmful consequences, giving a higher priority to drug use than other activities and obligations), and possible tolerance or physical dependence.

Abuse and misuse of barbiturates often (but not always) involve the use of doses exceeding the doses used in clinical practice and commonly involve concomitant use of other medications, alcohol, and/or illicit substances, which is associated with an increased frequency of serious adverse outcomes, including respiratory depression, overdose, or death. Barbiturates, including phenobarbital, are often sought by individuals who abuse drugs and other substances, and by individuals with addictive disorders.

Symptoms of acute intoxication with barbiturates include unsteady gait, slurred speech, and sustained nystagmus. Mental signs of chronic intoxication include confusion, poor judgment, irritability, insomnia, and somatic complaints. The use of phenobarbital alone can result in death; however, death is more often associated with phenobarbital use in the context of polysubstance use (especially with other CNS depressants, such as opioids and alcohol).

Phenobarbital may produce physical dependence. Physical dependence is a state that develops as a result of physiological adaptation in response to repeated drug use, manifested by withdrawal signs and symptoms after abrupt discontinuation or a significant dose reduction of a drug. Abrupt discontinuation or rapid dosage reduction of phenobarbital may precipitate acute withdrawal reactions, including seizures, which can be life-threatening.

Tolerance may occur with continued use. As tolerance to barbiturates develops, the amount needed to maintain the same level of intoxication increases; tolerance to a fatal dosage, however, does not increase more than twofold. As this occurs, the margin between intoxicating dosage and fatal dosage becomes smaller.

Consider the potential risks of misuse or abuse before prescribing this product. Signs of phenobarbital misuse or abuse include drug seeking behavior.

Diversion: FIDOQUEL™-CA1 is a Schedule IV antiepileptic and should be handled appropriately to minimize the risk of diversion, including restriction of access, the use of accounting procedures, and proper disposal methods. Store in a locked cabinet according to federal and state controlled substance requirements and guidelines. Any unused or expired bottles must be destroyed by a reverse distributor. For further information, contact your local DEA field office or call Genus Lifesciences Inc. at 1-833-599-7582.

Note to physician: FIDOQUEL™-CA1 contains phenobarbital.

Users can call Genus Lifesciences Inc. at 1-833-599-7582 at any time for product safety support. To obtain a Safety Data Sheet(s), contact Genus Lifesciences Inc. at 1-833-599-7582 or at https://www.genuslifesciences.com.

Animal Safety Warnings

Not for use in cats.

Do not use in pregnant or lactating dogs. Based on data from laboratory animals, administration of FIDOQUEL™-CA1 to pregnant dogs may produce congenital malformations in the developing fetus. Phenobarbital may be present and accumulate in the milk of lactating dogs.

Keep FIDOQUEL™-CA1 in a secure location out of the reach of dogs, cats, or other animals to prevent accidental ingestion or overdose.

PRECAUTIONS:

FIDOQUEL™-CA1 is for use in dogs 6 months of age and older.

The safe use of FIDOQUEL™-CA1 in neonates and young dogs has not been established.

Careful monitoring of therapeutic, biochemical, and hematology parameters is important in dogs receiving FIDOQUEL™-CA1. Dogs receiving FIDOQUEL™-CA1 should also be carefully monitored when administering concurrent medications.

Dogs with decreased liver function may be predisposed to phenobarbital toxicosis.

Some dogs may experience epileptic episodes that are refractory or unresponsive to FIDOQUEL™-CA1 monotherapy.

Dogs should be monitored for adverse events when adjusting the dose to determine the optimal dose for each patient.

The safe use of FIDOQUEL™-CA1 has not been evaluated in dogs that are intended for breeding, or that are pregnant or lactating.

ADVERSE REACTIONS:

Based on a comprehensive review of publications evaluating phenobarbital, the following adverse reactions are associated with administration of phenobarbital:

General: ataxia, lethargy, increased water consumption, increased appetite, increased urination, hyperactivity, vomiting, diarrhea, and weight gain.

Hematologic: increased serum alkaline phosphatase (ALP), increased serum alanine transferase (ALT), increased serum gamma-glutamyl transferase (GGT), decreased serum total and free thyroxine (T4) concentrations, immune-mediated anemia, neutropenia, and thrombocytopenia. Rarely, idiosyncratic hepatotoxicity may also occur.

A retrospective study of data on 1083 cases from a poison control center included 268 dogs that ingested phenobarbital alone at a dose of ≤5 mg/kg. Among the 22 dogs with at least one adverse reaction, the following were the most common adverse reactions observed: drowsiness/lethargy, ataxia, agitated/irritable, vocalization, unable to rise, and vomiting. Each of these adverse reactions were reported in 2 or more dogs.

CONTACT INFORMATION:

For a copy of the Safety Data Sheet (SDS) or to report suspected adverse drug experiences, contact Genus Lifesciences Inc. at 1-833-599-7582. For additional adverse drug experience reporting for animal drugs, contact FDA at 1-888-FDA-VETS or http://www.fda.gov/reportanimalae.

CLINICAL PHARMACOLOGY:

Mechanism of Action: Phenobarbital is a barbiturate thought to exert its antiepileptic activity by enhancing the action of gamma-aminobutyric acid (GABA) through binding to a site on the GABAA receptor/chloride channel. Barbiturates are also thought to decrease the influx of calcium into nerve cells and thereby decrease release of neurotransmitters.

PHARMACOKINETICS

Pharmacokinetics: The pharmacokinetics of phenobarbital in dogs have been described in published literature. Phenobarbital is considered a lipid-soluble drug exhibiting fast first-order absorption, high systemic availability, wide distribution, extensive hepatic metabolism, and slow and variable elimination from the body. Mean terminal elimination half-lives have been reported to range between 30 and 90 hours after oral administration.

Half-lives tend to decrease after weeks of continuous administration. Steady state concentrations are often achieved after 2 or more weeks of daily or twice daily dosing.

Phenobarbital has been reported to undergo self-induction of microsomal metabolism after weeks or months of daily administration, often requiring adjusting the dose after a certain period of time.

REASONABLE EXPECTATION OF EFFECTIVENESS:

A reasonable expectation of effectiveness may be demonstrated based on evidence such as, but not limited to, pilot data in the target species or studies from published literature.

FIDOQUEL™-CA1 (phenobarbital tablets) is conditionally approved pending a full demonstration of effectiveness.

Additional information for Conditional Approvals can be found at www.fda.gov/animalca

A reasonable expectation of effectiveness for FIDOQUEL™-CA1 for the control of seizures associated with idiopathic epilepsy in dogs is supported by eight publications in the scientific literature: two clinical consensus statements, and four prospective and two retrospective published studies.

The American College of Veterinary Medicine (ACVIM) 2016 clinical consensus statement on seizure management in dogs states that phenobarbital as monotherapy is likely to be effective based on evaluation of masked, randomized clinical trials. The ACVIM consensus statement reviewed 8 studies for a total of 311 dogs where seizure reduction was evaluated following phenobarbital monotherapy. Over the 8 studies, 82% of the dogs (258/311 dogs) had >50% seizure reduction, including 31% (93/311) that were seizure-free, and 15% (48/311) did not improve. The consensus statement recommends that phenobarbital should be orally administered at a starting dose of 2.5 mg/kg twice daily with adjustments based on each dog's clinical response and tolerance to the drug. The article stated that the most effective and safe therapeutic range is 15-35 µg/mL (serum concentration), although effectiveness can be seen at lower concentrations.

The International Veterinary Epilepsy Task Force (IVETF) consensus statement for the medical treatment of canine epilepsy in Europe states that phenobarbital has a favorable pharmacokinetic profile, is relatively safe, and, when serum phenobarbital concentration is maintained within the therapeutic range of 25-35 µg/mL, is 60-93% effective in decreasing seizure frequency in dogs with idiopathic epilepsy. The IVETF recommended an oral starting dose of 2.5-3 mg/kg twice daily, tailoring the dose to the individual dog based on seizure control, adverse effects, and serum concentration monitoring.

Four prospective studies support the reasonable expectation of effectiveness of FIDOQUEL™-CA1 for the control of seizures associated with idiopathic epilepsy in dogs. In one prospective study 15 dogs were treated with phenobarbital for at least 6 months. Twelve dogs (80%) showed ≥50% reduction in seizures, including 6 dogs (40%) who had no seizures during the study. In a second study, 17 of 20 dogs treated with phenobarbital had no seizures during the study (85%), and 18 showed a decrease in seizure duration (88%). In a third study, 88 dogs were treated with phenobarbital for at least 6 months, resulting in ≥50% reduction in seizure frequency in 73 dogs (83%), including 51 dogs (58%) who had no seizures during the study. In a fourth study, 5 out of 6 dogs treated with phenobarbital (83.3%) showed >50% reduction in seizures.

The results of two retrospective studies also support the reasonable expectation of effectiveness of FIDOQUEL™-CA1 for the control of seizures associated with idiopathic epilepsy in dogs. In one study, 11 out of 37 (30%) phenobarbital-treated Labrador retrievers had no seizures during the study, and an additional 16 out of 37 (43%) dogs showed decreased seizure frequency, severity, and/or duration. In another study, 28 of 44 (64%) phenobarbital-treated dogs had a ≥50% reduction in seizure frequency including 9 dogs (20%) who had no seizures during the study.

TARGET ANIMAL SAFETY:

A weight of evidence approach was used to determine the safety of FIDOQUEL™-CA1. The evidence included a 1, 3, 5× margin of safety study, an analysis of reports of phenobarbital exposure reported to an animal poison control center, and a critical review of publicly available literature regarding the use of phenobarbital in dogs. Safety was bridged between FIDOQUEL ™-CA1 and commercially available oral formulations of phenobarbital based upon published literature and formulation comparisons of qualitative, quantitative and dissolution data.

In the margin of safety study, FIDOQUEL™-CA1 was administered orally to dogs 1-2 years of age at 1, 3, and 5 times the maximum dose of 5 mg/kg every 12 hours. Beginning on the second day of dosing, 2 out of 8 dogs in the 3× group (15 mg/kg) and 7 out of 8 dogs in the 5× group (25 mg/kg) exhibited serious signs of toxicity, including significant sedation and ataxia. Due to the severity of the reactions, these seriously affected dogs were euthanized. The remaining dogs in the 3× and 5× groups had their doses reduced to 5 mg/kg. Due to the toxicity seen in the 3× and 5× groups the study was terminated early at 2 weeks.

In the retrospective study using an animal poison control center database, there were 1083 reports of dogs that ingested phenobarbital alone. Serious adverse events were reported in 50 of 1083 dogs (4.6%), and 43 of these 50 dogs received doses >25 mg/kg (>5× the highest recommended dose). The lowest dose associated with a serious adverse event was 14.29 mg/kg which represents a dose level of 2.86× the highest recommended dose. Serious adverse events included respiratory arrest, cardiac arrest, euthanasia, coma (unresponsive), and death.

In the systematic review of 30 scientific publications, administration of phenobarbital to dogs alone or in combination with other antiepileptic drugs resulted in adverse events including lethargy/sedation, ataxia, polyuria, polydipsia, polyphagia, weight gain, skin lesions (pruritus, alopecia, papules, pustules, erythema, and epidermal necrosis), changes in hematology parameters (neutropenia, anemia, thrombocytopenia), thyroid hormone changes (decreased thyroid hormone, increased TSH), and elevated liver enzymes including alanine aminotransferase (ALT), alkaline phosphatase (ALP), gamma glutamyl transferase (GGT), and glutamate dehydrogenase (GLDH). The liver enzyme elevations were generally attributed to enzyme induction rather than hepatotoxicity.

Phenobarbital-induced hematological abnormalities appear to be unrelated to dose. Lymphadenopathy, tremors, hypoadrenocortical crisis, and pancreatitis were also reported. Adverse effects were generally seen either soon after the start of treatment or when serum levels of phenobarbital were high (>35 mcg/ml). Some adverse events appeared to resolve or improve with time or when there is a reduction in the phenobarbital dose. Hepatotoxicity appeared to be associated with higher dosages and chronic phenobarbital use.

HOW SUPPLIED:

FIDOQUEL™-CA1 CIV tablets are unflavored, bisected tablets containing 15, 16.2, 30, 32.4, 60, 64.8, 97.2 and 100 mg phenobarbital per tablets. FIDOQUEL™-CA1 is packaged in bottles of 30, 100 or 1000 tablets.

STORAGE CONDITIONS:

Store at 25°C (77°F) with excursions permitted between 15 to 30°C (59 to 86°F).

Manufactured by:
Genus Lifesciences Inc.
Allentown, PA 18102

FIDOQUEL™ is a trademark of Genus Lifesciences Inc.

©2023 Genus. All rights reserved.

Rev. 01/25

PRINCIPAL DISPLAY PANEL - 15 mg Tablet Bottle Label

FIDOQUEL™-CA1
(phenobarbital tablets)
CIV

Antiepileptic for oral use in dogs only.

15 mg

Conditionally approved by FDA pending a
full demonstration of effectiveness under
application number 141-578. It is a violation
of federal law to use this product other than
as directed on the labeling.

Net Contents: 100 tablets

PRINCIPAL DISPLAY PANEL - 16.2 mg Tablet Bottle Label

FIDOQUEL™-CA1
(phenobarbital tablets)
CIV

Antiepileptic for oral use in dogs only.

16.2 mg

Conditionally approved by FDA pending a
full demonstration of effectiveness under
application number 141-578. It is a violation
of federal law to use this product other than
as directed on the labeling.

Net Contents: 100 tablets

PRINCIPAL DISPLAY PANEL - 30 mg Tablet Bottle Label

FIDOQUEL™-CA1
(phenobarbital tablets)
CIV

Antiepileptic for oral use in dogs only.

30 mg

Conditionally approved by FDA pending a
full demonstration of effectiveness under
application number 141-578. It is a violation
of federal law to use this product other than
as directed on the labeling.

Net Contents: 100 tablets

PRINCIPAL DISPLAY PANEL - 32.4 mg Tablet Bottle Label

FIDOQUEL™-CA1
(phenobarbital tablets)
CIV

Antiepileptic for oral use in dogs only.

32.4 mg

Conditionally approved by FDA pending a
full demonstration of effectiveness under
application number 141-578. It is a violation
of federal law to use this product other than
as directed on the labeling.

Net Contents: 100 tablets

PRINCIPAL DISPLAY PANEL - 60 mg Tablet Bottle Label

FIDOQUEL™-CA1
(phenobarbital tablets)
CIV

Antiepileptic for oral use in dogs only.

60 mg

Conditionally approved by FDA pending a
full demonstration of effectiveness under
application number 141-578. It is a violation
of federal law to use this product other than
as directed on the labeling.

Net Contents: 100 tablets

PRINCIPAL DISPLAY PANEL - 64.8 mg Tablet Bottle Label

FIDOQUEL™-CA1
(phenobarbital tablets)
CIV

Antiepileptic for oral use in dogs only.

64.8 mg

Conditionally approved by FDA pending a
full demonstration of effectiveness under
application number 141-578. It is a violation
of federal law to use this product other than
as directed on the labeling.

Net Contents: 100 tablets

PRINCIPAL DISPLAY PANEL - 97.2 mg Tablet Bottle Label

FIDOQUEL™-CA1
(phenobarbital tablets)
CIV

Antiepileptic for oral use in dogs only.

97.2 mg

Conditionally approved by FDA pending a
full demonstration of effectiveness under
application number 141-578. It is a violation
of federal law to use this product other than
as directed on the labeling.

Net Contents: 100 tablets

PRINCIPAL DISPLAY PANEL - 100 mg Tablet Bottle Label

FIDOQUEL™-CA1
(phenobarbital tablets)
CIV

Antiepileptic for oral use in dogs only.

100 mg

Conditionally approved by FDA pending a
full demonstration of effectiveness under
application number 141-578. It is a violation
of federal law to use this product other than
as directed on the labeling.

Net Contents: 100 tablets